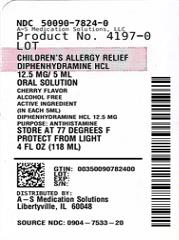 DRUG LABEL: Allergy Relief
NDC: 50090-7824 | Form: SOLUTION
Manufacturer: A-S Medication Solutions
Category: otc | Type: HUMAN OTC DRUG LABEL
Date: 20251218

ACTIVE INGREDIENTS: DIPHENHYDRAMINE HYDROCHLORIDE 12.5 mg/5 mL
INACTIVE INGREDIENTS: ANHYDROUS CITRIC ACID; AKA227; CURRY RED; GLYCERIN; HIGH FRUCTOSE CORN SYRUP; AQUA; SODIUM BENZOATE; SODIUM CHLORIDE; TRISODIUM CITRATE DIHYDRATE; SUCROSE

Major 44-015

Active ingredient (in each 5 mL)

Diphenhydramine HCl 12.5 mg

Purpose

Antihistamine

Uses

- temporarily relieves these symptoms due to hay fever or other upper respiratory allergies:
  - runny nose
  - sneezing
  - itchy, watery eyes
  - itching of the nose or throat

Warnings

Do not use

- to make a child sleepy
- with any other product containing diphenhydramine, even one used on skin

Ask a doctor before use if the child has

- glaucoma
- a breathing problem such as chronic bronchitis

Ask a doctor or pharmacist before use if the child is

taking sedatives or tranquilizers.

When using this product

- marked drowsiness may occur
- sedatives and tranquilizers may increase drowsiness
- excitability may occur, especially in children

Keep out of reach of children.

In case of overdose, get medical help or contact a Poison Control Center right away.

Directions

- do not take more than directed
- do not take more than 6 doses in 24 hours
- mL = milliliter
- only use the dose cup provided
- find right dose on chart below
- take every 4 to 6 hours, or as directed by a doctor

Age (yr) | Dose (mL)
children under 2 years | do not use
children 2 to 5 years | do not use unless directed by a doctor
children 6 to 11 years | 5 mL to 10 mL

Other information

- each 5 mL contains: sodium 4 mg
- store at 25°C (77°F); excursions permitted between 15°-30°C (59°-86°F)
- see end flap for expiration date and lot number
- protect from light

Inactive ingredients

anhydrous citric acid, D&C red #33, FD&C red #40, flavor, glycerin, high fructose corn syrup, purified water, sodium benzoate, sodium chloride, sodium citrate dihydrate, sucrose

Questions or comments?

1-800-426-9391

HOW SUPPLIED

Product: 50090-7824

NDC: 50090-7824-0 118 mL in a BOTTLE, PLASTIC / 1 in a CARTON